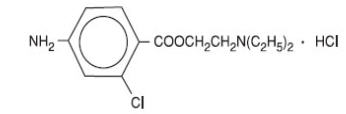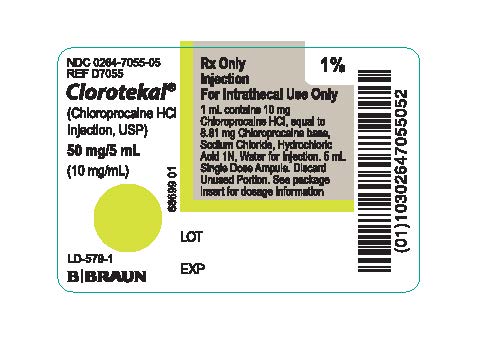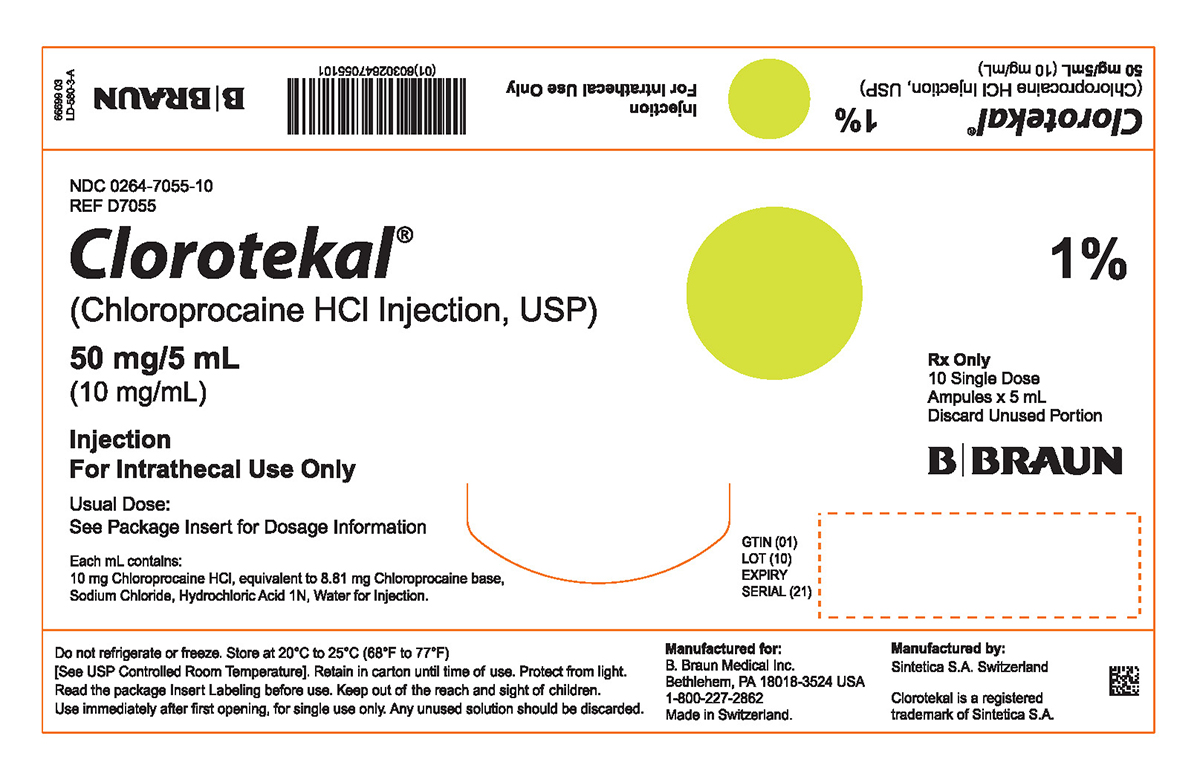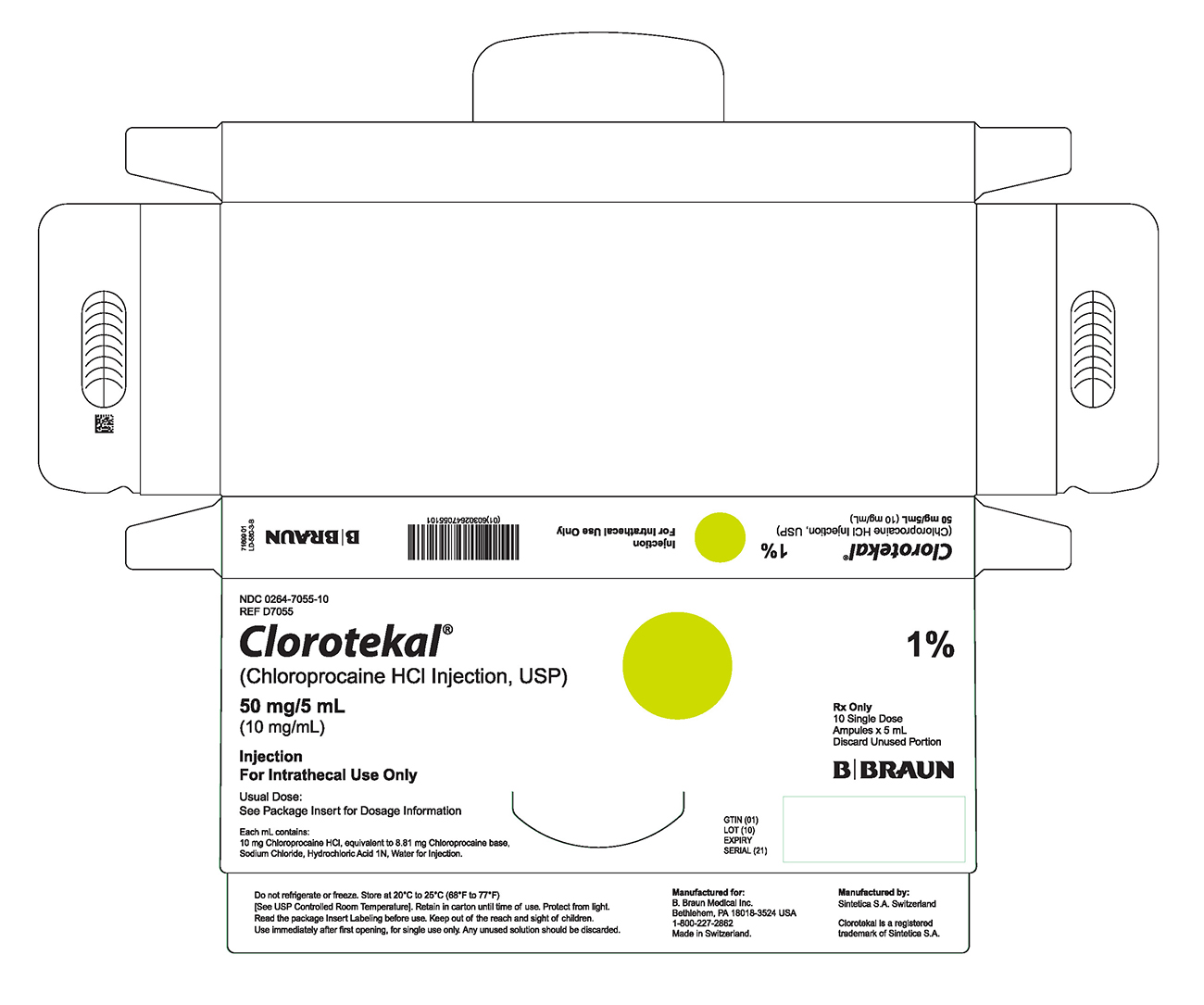 DRUG LABEL: Clorotekal
NDC: 0264-7055 | Form: INJECTION, SOLUTION
Manufacturer: B. Braun Medical Inc.
Category: prescription | Type: HUMAN PRESCRIPTION DRUG LABEL
Date: 20201204

ACTIVE INGREDIENTS: CHLOROPROCAINE HYDROCHLORIDE 10 mg/1 mL
INACTIVE INGREDIENTS: SODIUM CHLORIDE 7.2 mg/1 mL; HYDROCHLORIC ACID; WATER; NITROGEN

HIGHLIGHTS OF PRESCRIBING INFORMATION

These highlights do not include all the information needed to use CLOROTEKAL® safely and effectively. See full prescribing information for CLOROTEKAL®.
CLOROTEKAL® (chloroprocaine hydrochloride) injection for intrathecal use
Initial U.S. Approval: 1955

1 INDICATIONS AND USAGE

CLOROTEKAL® is an ester local anesthetic indicated for intrathecal injection in adults for the production of subarachnoid block (spinal anesthesia). (1)

2 DOSAGE AND ADMINISTRATION

CLOROTEKAL® is intended for single-dose administration only. (2.1)

To obtain an effective block to the T 10 level with one single administration in an adult of average height and weight (approximately 70 kg), the recommended dose is 50 mg (5 mL). (2.3)

3 DOSAGE FORMS AND STRENGTHS

5 mL Type I clear glass ampule contains 50 mg of chloroprocaine hydrochloride (10 mg/mL) equivalent to 44.05 mg/5 mL (8.81 mg/mL) chloroprocaine. (3)

4 CONTRAINDICATIONS

- Contraindicated in patients with a known hypersensitivity to the active substance, medicinal products of the PABA (para-aminobenzoic acid) ester group, other ester-type local anesthetics or to any of the excipients (4) (11)
- General and specific contra-indications to spinal anesthesia regardless of the local anesthetic used, should be taken into account (4)
- Intravenous regional anesthesia (4)
- Serious problems with cardiac conduction (4)
- Local infection at the site of proposed lumbar puncture (4)
- Septicemia. (4)

5 WARNINGS AND PRECAUTIONS

Risks with Neuraxial Administration: Local anesthetics should only be administered after insuring the immediate availability of oxygen, other resuscitative drugs, cardiopulmonary resuscitative equipment, and the personnel resources needed for proper management of toxic reactions and related emergencies. (5.1) (6) (10)

Cardiovascular System Reactions: hypotension and bradycardia. (5.2) (6) (10)

Central Nervous System Reactions: paresthesia, loss of sensitivity, motor weakness, paralysis, cauda equina syndrome and permanent neurological injury. (5.3) (6.2) (10)

Allergic Reactions: in patients with a known hypersensitivity to the active substance or to other formulation ingredients. (5.4) (6.2)

Chondrolysis: in intra-articular infusions in arthroscopic and other surgical procedures. (5.5)

6 ADVERSE REACTIONS

Adverse reactions reported with an incidence greater than or equal to 2 % following CLOROTEKAL® administration are procedural pain, injection site pain and hypotension. (6.1)

To report SUSPECTED ADVERSE REACTIONS, contact B. Braun Medical Inc. at 1-800-854-6851 or FDA at 1-800-FDA-1088 or www.fda.gov/medwatch.

7 DRUG INTERACTIONS

- Vasopressor and Ergot-Type Oxytocic Drugs: May cause severe, persistent hypertension or cerebrovascular accidents. Avoid concurrent administration (7)
- Sulfonamide Drugs: Avoid use in any condition in which a sulfonamide drug is being employed (7) (12.3)
- Antiarrhythmics: No studies have been performed on interactions between chloroprocaine and class III antiarrhythmics (e.g. amiodarone) (7)
- Local Anesthetics: Avoid combination of various local anesthetics. (7)

FULL PRESCRIBING INFORMATION

1 INDICATIONS AND USAGE

CLOROTEKAL® (chloroprocaine hydrochloride) is indicated for intrathecal injection for the production of subarachnoid block (spinal anesthesia) in adults undergoing surgical procedures. Indicated procedures include those suitable for CLOROTEKAL®'s short duration of action.

2 DOSAGE AND ADMINISTRATION

2.1 Important Dosage and Administration Information

CLOROTEKAL® must only be administered by clinicians with the necessary knowledge and experience in the intrathecal anesthesia administration. The equipment, drugs, and personnel capable of dealing with an emergency, e.g. maintaining the patency of the airways and administering oxygen, must be immediately available, because in rare cases severe reactions, sometimes with a fatal outcome, have been reported after using local anesthetics, even in the absence of individual hypersensitivity in the patient's case history.

- Visually inspect parental drug products for particulate matter and discoloration prior to administration, whenever solution and container permit.
- CLOROTEKAL® is intended for single-use only. Discard any unused portion in an appropriate manner.
- CLOROTEKAL® must be drawn up with a filter needle. Use CLOROTEKAL® immediately after first opening. Protect from light. Do not freeze, heat, or autoclave [see How Supplied/Storage and Handling (16)].
- In the absence of safety studies and compatibility studies, this product must not be mixed or diluted with other products. In addition, this product should not be substituted with a different chloroprocaine product.
- The safety of CLOROTEKAL® administration via continuous spinal catheters has not been established and administration by this route is not recommended.

2.2 Administration

Not for epidural administration.

Monitor vital signs during dural puncture and provide oxygen via face mask or nasal cannula. Slowly inject the entire dose, while monitoring the patient's vital signs.

In general, the following points should be taken into consideration:

- A free flow of cerebrospinal fluid during the performance of spinal anesthesia is indicative of entry into the subarachnoid space.
- To avoid intravascular injection, aspiration should be performed before the anesthetic solution is injected. The needle must be repositioned until no blood return can be elicited. However, the absence of blood in the syringe does not guarantee that intravascular injection has been avoided.
- Do not puncture the skin if there are signs of infection or inflammation.
- The patient should have IV fluids running via an indwelling catheter to assure functioning intravenous access.

2.3 Recommended Dosing

The extent and degree of spinal anesthesia depend upon several factors including dosage, specific gravity of the anesthetic solution, volume of solution used, force of injection, level of puncture, and position of the patient during and immediately after injection.

To obtain an effective block to the T 10 level with one single administration in an adult of average height and weight (approximately 70 kg), the recommended dose is 50 mg.

Doses above 50 mg have not been adequately tested for efficacy and safety.

3 DOSAGE FORMS AND STRENGTHS

CLOROTEKAL® is supplied as a single-dose sterile, clear, colorless solution in a Type I (USP) glass ampule that provides 50 mg of chloroprocaine hydrochloride in 5 mL aqueous solution (concentration: 10 mg/mL) equivalent to 44.05 mg/5 mL (8.81 mg/mL) chloroprocaine.

4 CONTRAINDICATIONS

- CLOROTEKAL® is contraindicated in patients with a known hypersensitivity to the active substance, medicinal products of the PABA (para-aminobenzoic acid) ester group, other ester-type local anesthetics or to any of the excipients [see Risk of Hypersensitivity Reactions (5.4)]
- General and specific contraindications to spinal anesthesia regardless of the local anesthetic used, should be taken into account (e.g., decompensated cardiac insufficiency, hypovolemic shock, coagulopathy)
- Intravenous regional anesthesia (the anesthetic agent is introduced into the limb and allowed to set in while tourniquets retain the agent within the desired area)
- Serious problems with cardiac conduction
- Local infection at the site of proposed lumbar puncture
- Septicemia

5 WARNINGS AND PRECAUTIONS

5.1 Risks with Neuraxial Administration

Local anesthetics should only be administered by clinicians who are well versed in diagnosis and management of dose-related toxicity and other acute emergencies which might arise from the block to be employed, and then only after insuring the immediate availability of oxygen, other resuscitative drugs, cardiopulmonary resuscitative equipment, and the personnel resources needed for proper management of toxic reactions and related emergencies [see Adverse Reaction (6) and Overdosage (10)]. Delay in proper management of dose-related toxicity, underventilation from any cause and/or altered sensitivity may lead to the development of acidosis, cardiac arrest, and, possibly, death.

The clinician should take the appropriate measures to avoid an intravascular injection [see Administration (2.2)]. In addition, it is essential for the clinician to know how to recognize and treat undesirable effects, systemic toxicity and other complications. If signs of acute systemic toxicity or total spinal block are observed, the injection of the local anesthetic must be stopped immediately [see Overdosage (10)].

5.2 Cardiovascular System Reactions

Hypotension and bradycardia are well known side effects of all local anesthetics [see Adverse Reaction (6) and Overdosage (10)].

A serious, undesirable effect of spinal anesthesia is high or total spinal block, with consequent cardiovascular and respiratory depression. Cardiovascular depression is induced by an extended block of the sympathetic nervous system, which may induce severe hypotension and bradycardia to the point of cardiac arrest. Respiratory depression is induced by the block of the respiratory musculature and the diaphragm. Careful and constant monitoring of cardiovascular and respiratory (adequacy of ventilation) vital signs and the patient's state of consciousness should be accomplished after CLOROTEKAL® injection.

Patients over 65 years, particularly those with hypertension, may be at increased risk for experiencing the hypotensive effects of CLOROTEKAL®. Blood pressure should, therefore, be carefully monitored after CLOROTEKAL® injection. Hypotension may be controlled by vasoconstrictors in dosages depending on the severity of hypotension and response of treatment.

5.3 Central Nervous System Reactions

Neurological damage may occur after spinal anesthesia, manifesting as paresthesia, loss of sensitivity, motor weakness, paralysis, cauda equina syndrome. Occasionally these symptoms persist and can be permanent. Carefully evaluate patients with underlying neuromuscular disorders and consider the risk-benefit ratio prior to treatment.

Carefully and constantly monitor cardiovascular and respiratory (adequacy of ventilation) vital signs and the patient's state of consciousness after local anesthetic injection. Restlessness, headache, anxiety, incoherent speech problems, lightheadedness, paresthesia, numbness and tingling of the mouth and lips, hearing problems, tinnitus, dizziness, blurred vision, convulsions, loss of consciousness tremors, depression, or drowsiness may be early warning signs of central nervous system toxicity [see Adverse Reactions (6.2) and Overdosage (10)].

5.4 Risk of Hypersensitivity Reactions

CLOROTEKAL® is contraindicated in patients hypersensitive to drugs of the PABA ester group. Allergic type reactions may occur as a result of sensitivity to the local anesthetic or to other formulation ingredients. These reactions are characterized by signs such as urticaria, pruritus, erythema, angioneurotic edema (including laryngeal edema), tachycardia, sneezing, nausea, vomiting, dizziness, syncope, excessive sweating, elevated temperature, and possibly, anaphylaxis type symptomatology (including severe hypotension). Cross sensitivity among members of the ester-type local anesthetic group has been reported. The usefulness of screening for sensitivity has not been definitely established [see Adverse Reactions (6.2)].

5.5 Risk of Chondrolysis in Patients Receiving Intraarticular Injections

Intra-articular infusions of local anesthetics following arthroscopic and other surgical procedures is an unapproved use and there have been post-marketing reports of chondrolysis in patients receiving such infusions. The majority of reported cases of chondrolysis have involved the shoulder joint; cases of gleno-humeral chondrolysis have been described in pediatric and adult patients following intra-articular infusions of local anesthetics with and without epinephrine for periods of 48 to 72 hours. There is insufficient information to determine whether shorter infusion periods are not associated with these findings. The time of onset of symptoms, such as joint pain, stiffness, and loss of motion, can be variable, but may begin as early as the 2nd month after surgery. Currently, there is no effective treatment for chondrolysis. Patients who experienced chondrolysis have required additional diagnostic and therapeutic procedures and some required arthroplasty or shoulder replacement.

5.6 Conditions Requiring Special Attention

Some patients require special attention in order to reduce the risk of serious undesirable effects, even when locoregional anesthesia constitutes the optimum choice for the surgical intervention:

- Patients with total or partial heart block, since local anesthetics can suppress myocardial conduction
- Patients with high grade cardiac decompensation
- Patients with advanced liver or kidney damage [see Use in Specific Populations (8.6)]
- Elderly patients and patients in poor general condition [see Use in Specific Populations (8.5) and Clinical Pharmacology (12.3)]
- Patients with genetic deficiency of plasma cholinesterase [see Adverse Reactions (6) and Clinical Pharmacology (12.3)]
- Patients taking anticoagulants or with congenital or acquired bleeding disorder
- Patients with severe anemia

Because ester-type local anesthetics are hydrolyzed by plasma cholinesterase produced by the liver, use CLOROTEKAL® cautiously in patients with advanced hepatic disease [see Use in Specific Populations (8.6)].

Local anesthetics should also be used with caution in patients with impaired cardiovascular function since they may be less able to compensate for functional changes associated with the prolongation of A-V conduction produced by these drugs.

6 ADVERSE REACTIONS

The following serious adverse reactions are described, or described in greater detail, in other sections:

- Cardiovascular System Reactions [see Warnings and Precautions (5.2)]
- Central Nervous System Reactions [see Warnings and Precautions (5.3)]
- Hypersensitivity Reactions [see Warnings and Precautions (5.4)]

6.1 Clinical Trials Experience

Because clinical studies are conducted under widely varying conditions, adverse reaction rates observed in the clinical trials of a drug cannot be directly compared to rates in the clinical studies of another drug and may not reflect the rates observed in practice.

During clinical investigations, a total of 111 patients undergoing various surgical procedures received CLOROTEKAL®. Patients were administered a dose ranging from 30 to 50 mg of CLOROTEKAL®.

Taking into consideration data for 50 mg dose only, the most common adverse reaction in these studies, (incidence greater than or equal to 10%) following CLOROTEKAL® administration was procedural pain.

The common adverse reactions (incidence greater than or equal to 2% to less than 10%) following CLOROTEKAL® administration were injection site pain and hypotension.

The less common/rare adverse reactions (incidence less than 2%) following CLOROTEKAL® administration were anesthetic complication, nausea, headache and hyperglycemia.

Adverse Reactions Reported in Controlled Trials

All Treatment Emergent Adverse Reactions in clinical studies comparing CLOROTEKAL® (dose 50 mg) to Bupivacaine 0.5% (10 mg) are shown in Table 1.

Table 1: Treatment-Emergent Adverse Events (TEAEs) in Controlled Trials (Phase 2 and Phase 3 Trials)
System Organ Class Preferred Term | Chloroprocaine 10 mg/mL (50 mg) N = 81 n (%) | Bupivacaine 0.5% (10 mg) N=64 n (%)
Subjects with Any TEAE | 17 (21.0) | 3 (4.7)
Injury, Poisoning and Procedural Complications | 13 (16.0) | 0 (0.0)
Procedural Pain | 13 (16.0) | 0 (0.0)
General Disorders and Administration Site Conditions | 3 (3.7) | 2 (3.1)
Injection Site Pain | 3 (3.7) | 2 (3.1)
Vascular Disorders | 4 (4.9) | 1 (1.6)
Hypotension | 4 (4.9) | 1 (1.6)
Note: Subjects are summarized according to the product they actually received. The denominator for calculating the proportions is the number of subjects in each treatment group and overall.
TEAE = Treatment-Emergent Adverse Event (both related and non-related).

6.2 Post-Marketing Experience

The following adverse reactions have been identified during post-approval of use of CLOROTEKAL® outside of the United States. Because these reactions are reported voluntarily from a population of uncertain size, it is not always possible to reliably estimate their frequency or establish a causal relationship to drug exposure (Table 2).

Table 2: Post-Marketing Reports of Adverse Drug Reactions
System Organ Class | Adverse Reactions
Immune System Disorders | Hypersensivity (including urticaria, pruritus, erythema multiforme, angioedema with possible airway obstruction), anaphylaxis
Injury, Poisoning and Procedural Complications | Urinary retention postoperative, delayed recovery from anesthesia, anesthetic complication
General Disorders and Administration Site Conditions | Feeling hot, malaise
Musculoskeletal and Connective Tissue Disorders | Back pain, groin pain, pain in extremity
Nervous System Disorders | Restlessness, paresthesia, dizziness, tremor, seizure, oral paresthesia, oral hypoesthesia, hearing disability, visual disorders, blurred vision, tinnitus, speech disorders, loss of consciousness, peripheral neuropathy, somnolence, unintentional total spinal block, urinary and anal incontinence, perineal disorder and sexual dysfunction, arachnoiditis, akathisia, presyncope, burning sensation, spinal cord injury, cauda equina syndrome, hypoesthesia, dysesthesia, motor dysfunction, myoclonus, phantom pain, headache
Eye Disorders | Diplopia, photophobia
Cardiac Disorders | Bradycardia, tachycardia, arrhythmia, myocardial depression, cardiac arrest
Psychiatric Disorders | Anxiety
Vascular Disorders | Hypertension, hypotension
Respiratory, Thoracic and Mediastinal Disorders | Respiratory depression, dyspnea, respiratory arrest
Gastrointestinal Disorders | Nausea, vomiting

7 DRUG INTERACTIONS

Concurrent administration of vasopressor drugs (for the treatment of hypotension related to obstetric blocks) and ergot-type oxytocic drugs may cause severe, persistent hypertension or cerebrovascular accidents.

The para-aminobenzoic acid metabolite of chloroprocaine inhibits the action of sulfonamides. Therefore, avoid use in any condition in which a sulfonamide drug is being employed [see Clinical Pharmacology (12.3)].

No studies have been performed on interactions between chloroprocaine and class III antiarrhythmics (e.g., amiodarone). Carefully monitor these patients for cardiovascular effects.

The combination of various local anesthetics may result in additive effects affecting the cardiovascular system and the central nervous system. Monitor these patients for signs and symptoms of local anesthetic toxicity.

8 USE IN SPECIFIC POPULATIONS

8.1 Pregnancy

Risk Summary

The limited available data with chloroprocaine use in pregnant women are insufficient to inform a drug associated risk of adverse developmental outcomes. There are no animal reproduction studies for chloroprocaine. There are risks to the mother and the fetus associated with use of chloroprocaine during labor and delivery (see Clinical Considerations).

The estimated background risk of major birth defects and miscarriage for the indicated population is unknown. All pregnancies have a background risk of birth defect, loss, or other adverse outcomes. In the U.S. general population, the estimated background risk of major birth defects and miscarriage in clinically recognized pregnancies is 2 to 4% and 15 to 20%, respectively.

Clinical Considerations

Labor or delivery

Local anesthetics rapidly cross the placenta, and when used for epidural, paracervical, pudendal or caudal block anesthesia, can cause varying degrees of maternal, fetal and neonatal toxicity [see Clinical Pharmacology (12.3)]. The incidence and degree of toxicity depend upon the procedure performed, the type and amount of drug used, and the technique of drug administration. Adverse reactions in the parturient, fetus and neonate involve alterations of the central nervous system, peripheral vascular tone and cardiac function.

Spinal anesthesia may alter the forces of parturition through changes in uterine contractility or maternal expulsive efforts. Spinal anesthesia has also been reported to prolong the second stage of labor by removing the parturient's reflex urge to bear down or by interfering with motor function. The use of obstetrical anesthesia may increase the need for forceps assistance.

The use of some local anesthetic drug products during labor and delivery may be followed by diminished muscle strength and tone for the first day or two of life.

Maternal hypotension has resulted from regional anesthesia. Local anesthetics produce vasodilation by blocking sympathetic nerves. The fetal heart rate also should be monitored continuously, and electronic fetal monitoring is highly advisable.

8.2 Lactation

Risk Summary

There are no data on the presence of chloroprocaine in human milk, the effects on the breastfed infant, or the effects on milk production.

The developmental and health benefits of breastfeeding should be considered along with the mother's clinical need for CLOROTEKAL® and any potential adverse effects on the breastfed infant from CLOROTEKAL® or from the underlying maternal condition.

8.4 Pediatric Use

Safety and effectiveness in pediatric patient have not been established.

8.5 Geriatric Use

Patients over 65 years, particularly those with hypertension, may be at increased risk of developing hypotension while undergoing spinal anesthesia with CLOROTEKAL®.

Clinical studies of CLOROTEKAL® did not include sufficient numbers of subjects 65 and over to determine whether they respond differently from younger subjects. Other reported clinical experience has not identified differences in responses between the elderly and younger patients. In general an elderly patient will have greater frequency of decreased hepatic, renal, or cardiac function, and of concomitant disease or other drug therapy [see Warnings and Precautions (5) and Clinical Pharmacology (12.3)].

8.6 Hepatic and Renal Impairment

Since ester-type local anesthetics are hydrolyzed by plasma cholinesterase produced by the liver, the risk of toxic reactions might be greater in patients with advanced hepatic disease [see Clinical Pharmacology (12.3)].

This drug and its metabolites are known to be substantially excreted by the kidney, and the risk of toxic reactions might be greater in patients with impaired renal function [see Clinical Pharmacology (12.3)].

10 OVERDOSAGE

Acute emergencies from local anesthetics are generally related to high plasma levels encountered during therapeutic use or to underventilation secondary to upward extension of spinal anesthesia. Hypotension is commonly encountered during the conduct of spinal anesthesia due to relaxation of sympathetic tone, and sometimes, contributory mechanical obstruction of venous return [see Warning and Precautions (5.1) and Adverse Reactions (6)].

In the case of accidental intravenous administration, the toxic effect occurs within 1 minute. In mice, the intravenous LD50 of chloroprocaine HCl is 97 mg/kg and the subcutaneous LD50 of chloroprocaine HCl is 950 mg/kg.

Management of Local Anesthetic Emergencies: the first consideration is prevention, best accomplished by careful and constant monitoring of cardiovascular and respiratory vital signs and the patient's state of consciousness after each local anesthetic injection. At the first sign of change, administration of CLOROTEKAL® must be stopped and oxygen should be administered [see Warning and Precautions (5.1)].

The first step in the management of convulsions, as well as underventilation or apnea, consists of immediate attention to the maintenance of a patient airway and assisted or controlled ventilation with oxygen and a delivery system capable of permitting immediate positive airway pressure by mask. Immediately after the institution of these ventilatory measures, the adequacy of the circulation should be evaluated, keeping in mind that drugs used to treat convulsions sometimes depress the circulation when administered intravenously. Should convulsions persist despite adequate respiratory support, and if the status of the circulation permits, small increments of an ultra-short acting barbiturate or a benzodiazepine may be administered intravenously; the clinician should be familiar, prior to the use of anesthetics, with appropriate anticonvulsant drugs. Supportive treatment of circulatory depression may require administration of intravenous fluids and, when appropriate, a vasopressor dictated by the clinical situation (such as ephedrine to enhance myocardial contractile force). If not treated immediately, both convulsions and cardiovascular depression can result in hypoxia, acidosis, bradycardia, arrhythmias and cardiac arrest. Recovery has been reported after prolonged resuscitative efforts. Endotracheal intubation, employing drugs and techniques familiar to the clinician, may be indicated, after initial administration of oxygen by mask, if difficulty is encountered in the maintenance of a patient's airway or if prolonged ventilatory support (assisted or controlled) is indicated.

11 DESCRIPTION

CLOROTEKAL® is a sterile non pyrogenic local anesthetic.

The active ingredient in CLOROTEKAL® is chloroprocaine hydrochloride (benzoic acid, 4-amino-2-chloro-2-(diethylamino) ethyl ester, monohydrochloride), an ester local anesthetic, which is represented by the following structural formula:

1 mL of solution for injection contains 10 mg of chloroprocaine hydrochloride, equivalent to 44.05 mg/5 mL (8.81 mg/mL) chloroprocaine. It also contains the following inactive ingredients: hydrochloric acid 1N (for pH adjustment), sodium chloride, water for injection. The pH of the solution is between 3.0 and 4.0. The osmolality of the solution is 270 – 300 mOsm/kg.

12 CLINICAL PHARMACOLOGY

12.1 Mechanism of Action

Chloroprocaine, like other local anesthetics, blocks the generation and the conduction of nerve impulses, presumably by increasing the threshold for electrical excitation in the nerve, by slowing the propagation of the nerve impulse and by reducing the rate of rise of the action potential. In general, the progression of anesthesia is related to the diameter, myelination and conduction velocity of affected nerve fibers. Clinically, the order of loss of nerve function is as follows: (1) pain, (2) temperature, (3) touch, (4) proprioception, and (5) skeletal muscle tone.

12.2 Pharmacodynamics

Systemic absorption of local anesthetics produces effects on the cardiovascular and central nervous systems. At blood concentrations achieved with normal therapeutic doses, changes in cardiac conduction, excitability, refractoriness, contractility, and peripheral vascular resistance are minimal. However, toxic blood concentrations depress cardiac conduction and excitability, which may lead to atrioventricular block and ultimately to cardiac arrest. In addition, with toxic blood concentrations myocardial contractility may be depressed and peripheral vasodilation may occur, leading to decreased cardiac output and arterial blood pressure.

Following systemic absorption, toxic blood concentrations of local anesthetics can produce central nervous system stimulation, depression, or both. Apparent central stimulation may be manifested as restlessness, tremors and shivering, which may progress to convulsions. Depression and coma may occur, possibly progressing ultimately to respiratory arrest.

However, the local anesthetics have a primary depressant effect on the medulla and on higher centers. The depressed stage may occur without a prior stage of central nervous system stimulation.

12.3 Pharmacokinetics

The rate of systemic absorption of local anesthetic drugs is dependent upon the total dose concentration of drug administered, the route of administration, the vascularity of the administration site, and the presence or absence of epinephrine in the anesthetic injection.

The onset of action with chloroprocaine is rapid (usually 6 to 12 minutes), and the duration of anesthesia, depending upon the amount used and the route of administration.

Local anesthetics appear to cross the placenta by passive diffusion. However, the rate and degree of diffusion varies considerably among the different drugs as governed by: (1) the degree of plasma protein binding, (2) the degree of ionization, and (3) the degree of lipid solubility.

Fetal/maternal ratios of local anesthetics appear to be inversely related to the degree of plasma protein binding, since only the free, unbound drug is available for placental transfer. Thus, drugs with the highest protein binding capacity may have the lowest fetal/maternal ratios. The extent of placental transfer is also determined by the degree of ionization and lipid solubility of the drug. Lipid soluble, nonionized drugs readily enter the fetal blood from the maternal circulation.

Distribution

Depending upon the route of administration, local anesthetics are distributed to some extent to all body tissues, with high concentrations found in highly perfused organs such as the liver, lungs, heart, and brain. Various pharmacokinetic parameters of the local anesthetics can be significantly altered by the presence of hepatic or renal disease, addition of epinephrine, factors affecting urinary pH, renal blood flow, the route of administration, and the age of the patient.

Chloroprocaine plasma half-life in vitro is about 25 seconds, whereas the apparent half-life in vivo was found to be 3.1±1.6 min (range 1.5 to 6.4 min) in maternal plasma after intrapartum epidural anesthesia.

Metabolism

Chloroprocaine is rapidly metabolized in plasma by hydrolysis of the ester linkage by pseudocholinesterase. The hydrolysis of chloroprocaine results in the production of ß-diethylaminoethanol and 2-chloro-4-aminobenzoic acid, which inhibits the action of the sulfonamides [see Drug Interactions (7)].

Excretion

The kidney is the main excretory organ for most local anesthetics and their metabolites. Urinary excretion is affected by urinary perfusion and factors affecting urinary pH.

Pharmacokinetic after intrathecal administration

Plasma concentrations of chloroprocaine and 2-chloro-4-aminobenzoic acid (ACBA) after intrathecal administration of 50 mg dose of CLOROTEKAL® are reported in Table 3.

Table 3 - PK Variables: Plasma Concentrations (ng/mL) of chloroprocaine and ACBA
Analyte | chloroprocaine | ACBA
Dose group | 50 mg | 50 mg
 | N=15 | N=15
Pre-dose (0) | BLQL | BLQL
5 min post-dose | BLQL | 24.9±20.3
10 min post-dose | BLQL | 75.8±67.6
30 min post-dose | BLQL | 97.6±61.7
60 min post-dose | BLQL | 78.4±48.4
Mean ± SD is shown; BLQL: below the quantification limit (4.0 ng/mL)

Specific Populations

Renal Impairment

Chloroprocaine is known to be substantially excreted by the kidney [see Warnings and Precautions (5.1) and Use in Specific Populations (8.6)].

13 NONCLINICAL TOXICOLOGY

13.1 Carcinogenesis, Mutagenesis, Impairment of Fertility

Carcinogenesis

Long-term studies in animals to evaluate carcinogenic potential of chloroprocaine have not been conducted.

Mutagenesis

2-chloroprocaine and the main metabolite, ACBA, were negative in the in vitro bacterial reverse mutation test (Ames assay) and the in vitro chromosome aberrations assay.

Impairment of Fertility

Studies in animals to evaluate the impairment of fertility have not been conducted with chloroprocaine.

14 CLINICAL STUDIES

14.1 Study 1

A Phase 2 single-center, prospective, randomized, observer-blind study evaluated the efficacy and the tolerability of chloroprocaine 30, 40, and 50 mg after spinal injection in 45 patients (27 males and 18 females) undergoing short duration (< 40 minutes) lower limb surgery. The mean age was 41 years (range 19 to 63).

Efficacy was determined by proportion of patients who were able to complete the surgical procedure without the need for supplementary intravenous analgesic or sedation drugs.

Efficacy results

Neither rescue anesthesia nor rescue analgesia was required for subjects randomized to chloroprocaine 50 mg. Three subjects in the 30 mg dose group and three subjects in the 40 mg dose group required intraoperative rescue medications. Duration data such as time from injection to surgery end, etc., for the chloroprocaine 50 mg-administered subjects follow:

Table 4 – Duration Data for Chloroprocaine 50 mg Subjects in Minutes (N = 15)
 | Mean | Median | Minimum | Maximum
Time from injection to surgery start | 22 | 20 | 11 | 42
Time from injection to surgery end | 41 | 40 | 24 | 60
Time from injection to resolution of motor block | 100 | 104 | 56 | 146
Time from surgery start to surgery finish | 20 | 20 | 5 | 40

The maximum surgical duration in the 50 mg dose group was 40 minutes and 93% (14 of 15) of the 50 mg dose group had surgical procedures ≤ 30 minutes.

14.2 Study 2

A Phase 3, multicenter, prospective, randomized, observer-blind study evaluated the safety and the efficacy of 50 mg of chloroprocaine 10 mg/mL in intrathecal anesthesia versus 10 mg of bupivacaine 0.5%, in 130 patients (69 males and 61 females) undergoing short duration (< 40 minutes) low abdominal surgery (gynecological or urological) and lower limb surgery that required T10 metameric level of sensory block and identical anesthesia procedures.

The mean age was 45 years (range 18 to 78) in the chloroprocaine group and 51 years (range 20 to 79) in the bupivacaine group. Each patient received a single dose of anesthetic (50 mg of chloroprocaine or 10 mg of bupivacaine) according to the randomization plan. Sixty-six subjects were randomized to the chloroprocaine group. Sixty-four subjects were randomized to the bupivacaine group.

Efficacy was determined by proportion of patients who were able to complete the surgical procedure without the need for rescue intravenous analgesic or sedation drugs.

Efficacy results

Six of 66 subjects (9%) in the chloroprocaine group required rescue compared to 6 of 64 (9%) in the bupivacaine group. Duration data such as time from injection to surgery end, etc., for the chloroprocaine-administered subjects follow:

Table 5 – Duration Data in Minutes (N = 66)
 | Mean | Median | Minimum | Maximum
Time from injection to surgery start | 16 | 15 | 3 | 42
Time from injection to surgery end | 39 | 34 | 9 | 90
Time from injection to resolution of motor block | 101 | 100 | 40 | 194
Time from surgery start to surgery finish | 23 | 20 | 3 | 78

Only two subjects had surgical procedures lasting over 60 minutes, and both required intraoperative rescue medications.

16 HOW SUPPLIED/STORAGE AND HANDLING

The CLOROTEKAL® is supplied as a 50mg/5mL (10 mg/mL) equivalent to 44.05 mg/5 mL (8.81 mg/mL) chloroprocaine Type I glass ampules, stored in cartons containing 10 single-dose ampules.

NDC | REF | Size
0264-7055-10 | D7055 | 5mL

The product is intended for intrathecal administration.

Solutions which are discolored or which contain particulate matter should not be administered.

Handling

- Ampule should be visually inspected before use
- Protect from light
- Store in Carton
- Do not refrigerate or freeze
- Do not heat before use
- Do not autoclave
- The medicinal product has to be used immediately after first opening
- Discard any unused portion in an appropriate manner.

Storage

Store at 20°C to 25°C (68°F to 77°F); excursions permitted between 15°C to 30°C (59°F to 86°F).

17 PATIENT COUNSELING INFORMATION

Inform patients in advance that chloroprocaine-containing products can cause temporary loss of sensation or motor activity, usually in the lower half of the body, following proper administration of spinal anesthesia.

Rx only

Clorotekal® is a registered trademark of Sintetica S.A.

Manufactured by:
Sintetica S.A.
Switzerland

Manufactured for:
B. Braun Medical Inc.
Bethlehem, PA 18018-3524 USA
1-800-227-2862

Made in Switzerland

LD-578-1

PRINCIPAL DISPLAY PANEL - 5 mL Ampule Label

NDC 0264-7055-05
REF D7055

Clorotekal®

(Chloroprocaine HCl
Injection, USP)

50 mg/5 mL
(10 mg/mL)

LD-579-1

Rx Only
Injection
For Intrathecal Use Only
1 mL contains 10 mg Chloroprocaine HCI, equal to 8.81 mg Chloroprocaine base, Sodium Chloride, Hydrochloric Acid 1N, Water for Injection. 5 mL Single Dose Ampule. Discard Unused Portion. See package insert for dosage information

68699 01

LOT

EXP

1%

PRINCIPAL DISPLAY PANEL - 5 mL Ampule Carton (A)

NDC 0264-7055-10
REF D7055

Clorotekal®

(Chloroprocaine HCl Injection, USP)

50 mg/5 mL
(10 mg/mL)

Injection
For Intrathecal Use Only

Usual Dose:
See Package Insert for Dosage Information

Each mL contains:
10 mg Chloroprocaine HCl, equivalent to 8.81 mg Chloroprocaine base,
Sodium Chloride, Hydrochloric Acid 1N, Water for Injection.

1%

Rx Only
10 Single Dose
Ampules x 5 mL
Discard Unused Portion

GTIN (01)
LOT (10)
EXPIRY
SERIAL (21)

Do not refrigerate or freeze. Store at 20°C to 25°C (68°F to 77°F)
[See USP Controlled Room Temperature]. Retain in carton until time of use. Protect from light. Read the package Insert Labeling before use. Keep out of the reach and sight of children. Use immediately after first opening, for single use only. Any unused solution should be discarded.

Manufactured for:
B. Braun Medical Inc.
Bethlehem, PA 18018-3524 USA
1-800-227-2862
Made in Switzerland.

Manufactured by:
Sintetica S.A. Switzerland

Clorotekal is a registered trademark of Sintetica S.A.

66699 03
LD-580-3-A

LD-580-3-A

PRINCIPAL DISPLAY PANEL - 5 mL Ampule Carton (B)

NDC 0264-7055-10
REF D7055

Clorotekal®

(Chloroprocaine HCl Injection, USP)

50 mg/5 mL
(10 mg/mL)

Injection
For Intrathecal Use Only

Usual Dose:
See Package Insert for Dosage Information

Each mL contains:
10 mg Chloroprocaine HCl, equivalent to 8.81 mg Chloroprocaine base,
Sodium Chloride, Hydrochloric Acid 1N, Water for Injection.

1%

Rx Only
10 Single Dose
Ampules x 5 mL
Discard Unused Portion

GTIN (01)
LOT (10)
EXPIRY
SERIAL (21)

Do not refrigerate or freeze. Store at 20°C to 25°C (68°F to 77°F)
[See USP Controlled Room Temperature]. Retain in carton until time of use. Protect from light. Read the package Insert Labeling before use. Keep out of the reach and sight of children. Use immediately after first opening, for single use only. Any unused solution should be discarded.

Manufactured for:
B. Braun Medical Inc.
Bethlehem, PA 18018-3524 USA
1-800-227-2862
Made in Switzerland.

Manufactured by:
Sintetica S.A. Switzerland

Clorotekal is a registered trademark of Sintetica S.A.

66699 03
LD-580-3-B

LD-580-3-B